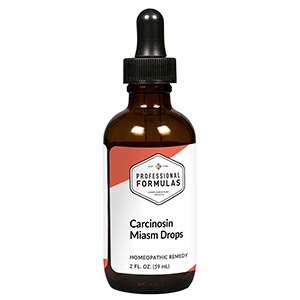 DRUG LABEL: Carcinosin Miasm Drops
NDC: 63083-2142 | Form: LIQUID
Manufacturer: Professional Complementary Health Formulas
Category: homeopathic | Type: HUMAN OTC DRUG LABEL
Date: 20190815

ACTIVE INGREDIENTS: GOLD TRICHLORIDE 6 [hp_X]/59 mL; COMFREY ROOT 6 [hp_X]/59 mL; HEKLA LAVA 8 [hp_X]/59 mL; LACTIC ACID, L- 15 [hp_X]/59 mL; ASTERIAS RUBENS 30 [hp_X]/59 mL; CROTALUS HORRIDUS HORRIDUS VENOM 30 [hp_X]/59 mL; THUJA OCCIDENTALIS LEAF 30 [hp_X]/59 mL; CLAVICEPS PURPUREA SCLEROTIUM 60 [hp_X]/59 mL; MELANDRIN 100 [hp_X]/59 mL; HUMAN BREAST TUMOR CELL 100 [hp_X]/59 mL; ARSENIC TRIOXIDE 200 [hp_X]/59 mL; LIQUID PETROLEUM 200 [hp_X]/59 mL; SULFUR 200 [hp_X]/59 mL
INACTIVE INGREDIENTS: ALCOHOL; WATER

C142

ACTIVE INGREDIENTS

Aurum muriaticum 6X
Symphytum officinale 6X
Hekla lava 8X
Sarcolacticum acidum 15X
Asterias rubens 30X
Crotalus horridus 30X
Thuja occidentalis 30X
Secale cornutum 60X
Malandrinum 100X
Carcinosin 100X, 200X
Arsenicum album 200X
Petroleum 200X
Sulphur 200X

QUESTIONS

Professional Formulas

PO Box 2034 Lake Oswego, OR 97035

INDICATIONS

For the temporary relief of fatigue, insomnia, sinusitis or other upper respiratory allergies, or suppression of emotions consistent with classical carcinosin miasm.*

PURPOSE

*Claims based on traditional homeopathic practice, not accepted medical evidence. Not FDA evaluated.

WARNINGS

In case of overdose, get medical help or contact a poison control center right away.

Keep out of the reach of children.

PREGNANCY OR BREAST FEEDING

If pregnant or breastfeeding, ask a healthcare professional before use.

DIRECTIONS

Place drops under tongue 30 minutes before/after meals. Adults and children 12 years and over: Take 10 drops up to 3 times per day. Consult a physician for use in children under 12 years of age.

OTHER INFORMATION

Tamper resistant. If seal is broken, do not use. After opening, close container tightly and store at room temperature away from heat.

INACTIVE INGREDIENTS

20% ethanol, purified water.

LABEL

Est 1985

Professional Formulas

Complementary Health

Carcinosin Miasm Drops

Homeopathic Remedy

2 FL. OZ. (59 mL)